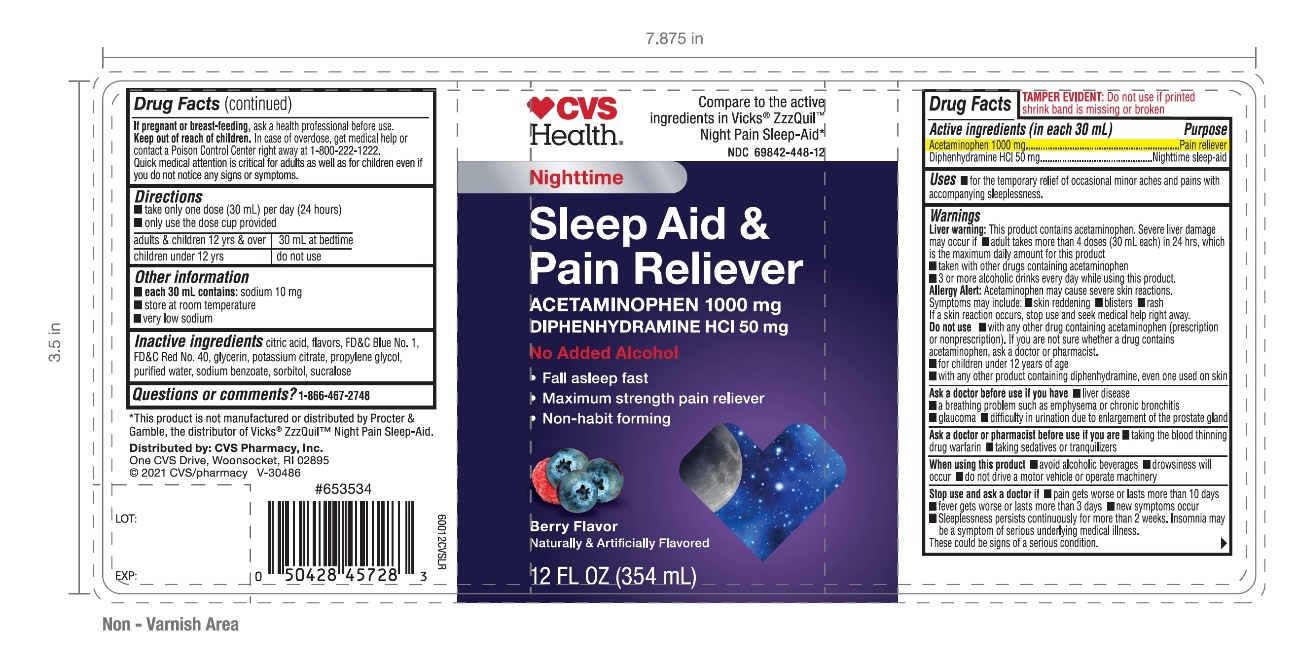 DRUG LABEL: CVS Nighttime

NDC: 69842-448 | Form: LIQUID
Manufacturer: CVS PHARMACY
Category: otc | Type: HUMAN OTC DRUG LABEL
Date: 20251208

ACTIVE INGREDIENTS: ACETAMINOPHEN 1000 mg/30 mL; DIPHENHYDRAMINE HYDROCHLORIDE 50 mg/30 mL
INACTIVE INGREDIENTS: CITRIC ACID MONOHYDRATE; FD&C BLUE NO. 1; FD&C RED NO. 40; GLYCERIN; POTASSIUM CITRATE; PROPYLENE GLYCOL; WATER; SODIUM BENZOATE; SORBITOL; SUCRALOSE

CVS Nighttime Sleep-aid Pain Reliever

Drug Facts

Active ingredients (in each 30 mL)

Acetaminophen 1000 mg

Diphenhydramine HCl 50 mg

Purpose

Pain reliever

Nighttime sleep-aid

Uses

- for the temporary relief of occasional minor aches and pains with accompanying sleeplessness.

Warnings

Liver warning: This product contains acetaminophen. Severe liver damage may occur if

- adult takes more than 4 doses (30 mL each) in 24 hrs., which is the maximum daily amount for this product
- taken with other drugs containing acetaminophen
- 3 or more alcoholic drinks every day while using this product

Allergy Alert: Acetaminophen may cause severe skin reactions.

Symptoms may include:

- skin reddening
- blisters
- rash

If a skin reaction occurs, stop use and seek medical help right away

Do not use

- with any other drug containing acetaminophen (prescription or nonprescription). If you are not sure whether a drug contains acetaminophen, ask a doctor or pharmacist.
- for children under 12 years of age
- with any other product containing diphenhydramine, even one used on skin.

Ask a doctor before use if you have

- liver disease
- a breathing problem such as emphysema or chronic bronchitis
- glaucoma
- difficulty in urination due to enlargement of the prostate gland

Ask a doctor or pharmacist before use if you are

- taking the blood thinning drug warfarin
- taking sedatives or tranquilizers

When using this product

- avoid alcoholic beverages
- drowsiness will occur
- do not drive a motor vehicle or operate machinery

Stop use and ask a doctor if

- pain gets worse or lasts more than 10 days
- fever gets worse or lasts more than 3 days
- new symptoms occur
- Sleeplessness persists continuously for more than 2 weeks. Insomnia may be a symptom of serious underlying medical illness.

These could be signs of a serious condition.

PREGNANCY OR BREAST FEEDING

If pregnant or breast-feeding, ask a health professional before use.

Keep out of reach of children.In case of overdose, get medical help or contact a Poison Control Center right away at 1-800-222-1222. Quick medical attention is critical for adults as well as for children even if you do not notice any signs or symptoms.

Directions

- take only one dose (30 mL) per day (24 hours)
- Only use dose cup provided

adults & children 12 yrs & over | 30 mL at bedtime
children under 12 yrs | do not use

Other information

- each 30 mL contains:sodium 10 mg
- store at room temperature
- very low sodium

Inactive ingredients

citric acid, flavors, FD&C Blue No. 1, FD&C Red No. 40, glycerin, potassium citrate, propylene glycol, purified water, sodium benzoate, sorbitol, sucralose.

Questions or comments?

1-866-467-2748

PRINCIPAL DISPLAY PANEL - 354 ml bottle

Compare to the active ingredient in Vicks® ZzzQuil™ Night Pain Sleep-Aid*

NDC# 69842-448-12

Nighttime Sleep-Aid

Pain Reliever
Diphenhydramine HCl

Acetaminophen

- Fall Asleep Fast
- Max Strength Pain Reliever
- Non-Habit Forming

Berry Flavor

Naturally and Artificially Flavored

No Added Alcohol

12 FL. OZ. (354 ml)

*This product is not manufactured or distributed by Procter & Gamble, the distributor of Vicks® ZzzQuil™ Nigh Pain Sleep-Aid.

Distributed by: